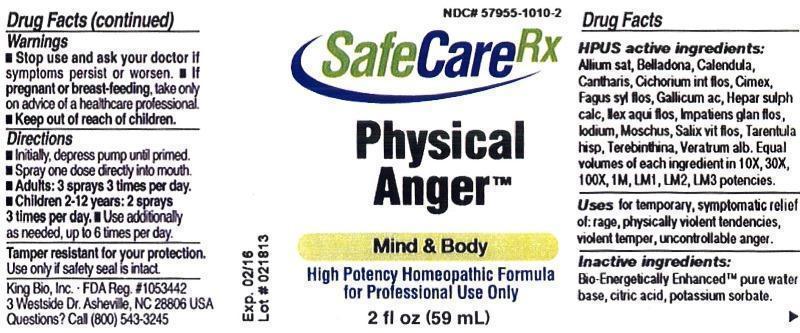 DRUG LABEL: Physical Anger
NDC: 57955-1010 | Form: LIQUID
Manufacturer: King Bio Inc.
Category: homeopathic | Type: HUMAN PRESCRIPTION DRUG LABEL
Date: 20130416

ACTIVE INGREDIENTS: GARLIC 10 [hp_X]/59 mL; ATROPA BELLADONNA 10 [hp_X]/59 mL; CALENDULA OFFICINALIS FLOWERING TOP 10 [hp_X]/59 mL; LYTTA VESICATORIA 10 [hp_X]/59 mL; CICHORIUM INTYBUS FLOWER 10 [hp_X]/59 mL; CIMEX LECTULARIUS 10 [hp_X]/59 mL; FAGUS SYLVATICA FLOWERING TOP 10 [hp_X]/59 mL; GALLIC ACID MONOHYDRATE 10 [hp_X]/59 mL; CALCIUM SULFIDE 10 [hp_X]/59 mL; ILEX AQUIFOLIUM FLOWERING TOP 10 [hp_X]/59 mL; IMPATIENS GLANDULIFERA FLOWER 10 [hp_X]/59 mL; IODINE 10 [hp_X]/59 mL; MOSCHUS MOSCHIFERUS MUSK SAC RESIN 10 [hp_X]/59 mL; SALIX ALBA FLOWERING TOP 10 [hp_X]/59 mL; LYCOSA TARANTULA 10 [hp_X]/59 mL; TURPENTINE OIL 10 [hp_X]/59 mL; VERATRUM ALBUM ROOT 10 [hp_X]/59 mL
INACTIVE INGREDIENTS: WATER; CITRIC ACID MONOHYDRATE; POTASSIUM SORBATE

Physical Anger

Warnings

- Stop use and ask your doctor if symptoms persist or worsen.
- If pregnant or breast-feeding, take only on advice of a healthcare professional.
- Keep out of reach of children.

Tamper resistant for your protection. Use only if safety seal is intact.

Keep out of reach of children.

Directions

- Initially, depress pump until primed.
- Spray one dose directly into mouth.
- Adults: 3 sprays 3 times per day.
- Children 2-12 years: 2 sprays 3 times per day.
- Use additionally as needed, up to 6 times per day.

HPUS Active Ingredients

Allium sativum, Belladonna, Calendula officinalis, Cantharis, Cichorium intybus, flos, Cimex lectularius, Fagus sylvatica, flos, Gallicum acidum, Hepar sulphuris calcareum, Ilex aquifolium, flos, Impatiens glandulifera, flos, Iodium, Moschus, Salix vitellina, flos, Tarentula hispana, Terebinthina, Veratrum album.

Equal volumes of each ingredient in 10X, 30X, 100X, 1M, LM1, LM2, LM3 potencies.

Indications and Usage

Uses for temporary, symptomatic relief of: rage, physically violent tendencies, violent temper, uncontrollable anger.

Inactive Ingredients

Bio-Energetically Enhanced™ pure water base, citric acid, potassium sorbate.

Purpose

Uese for temporary, symptomatic relief of:

- rage
- physically violent tendencies
- violent temper
- uncontrollable anger